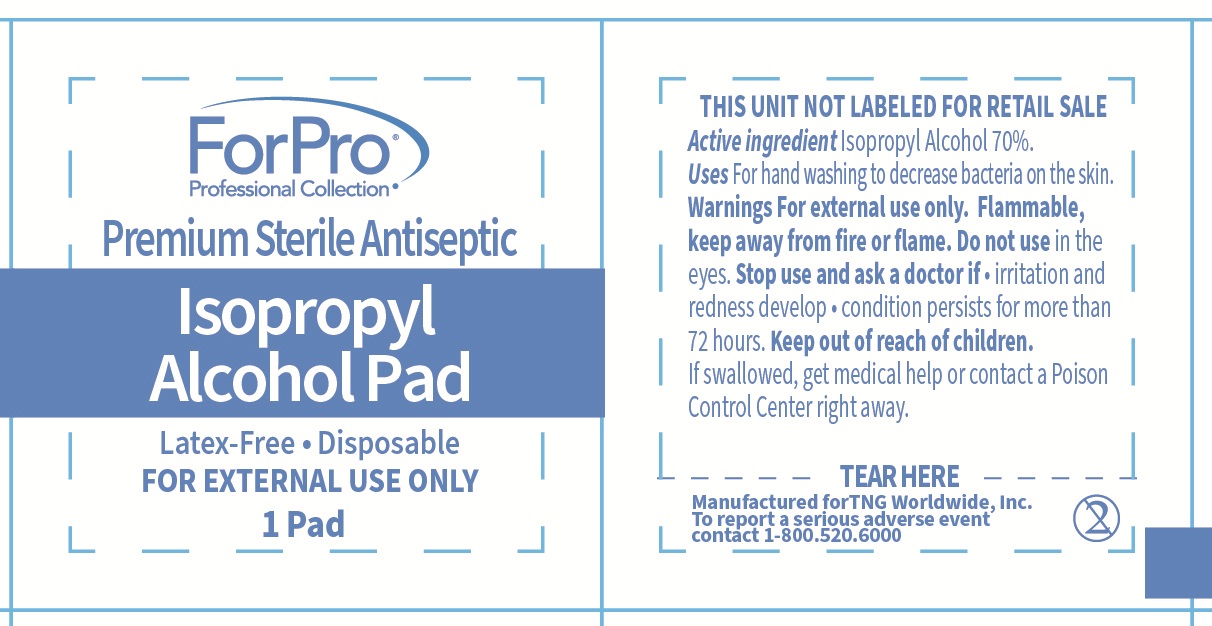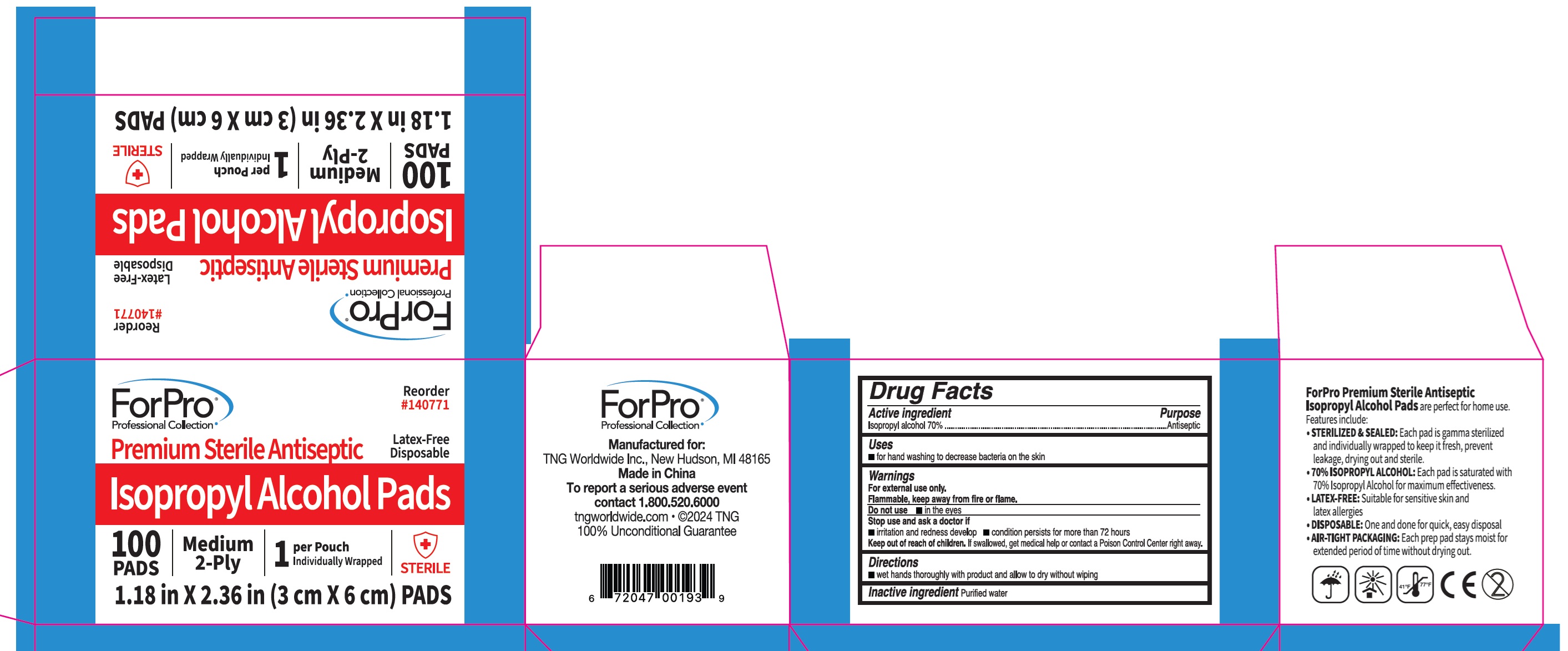 DRUG LABEL: ForPro Premium Sterile Antiseptic Isopropyl Alcohol Pads
NDC: 84974-001 | Form: SWAB
Manufacturer: Tng workdwide
Category: otc | Type: HUMAN OTC DRUG LABEL
Date: 20260205

ACTIVE INGREDIENTS: ISOPROPYL ALCOHOL 70 mL/100 mL
INACTIVE INGREDIENTS: WATER

For Pro Premium Sterile Antiseptic Isopropyl Alcohol Pads

Active ingredient

Isopropyl alcohol 70%

Purpose

Antiseptic

Uses

- for hand washing to decrease bacteria on the skin

Warnings

For external use only.

Flammable, keep away from fire or flame.

Do not use

- in the eyes.

Stop use and ask a doctor if

- irritation and redness develop
- condition persists for more than 72 hours

Keep out of reach of children.

If swallowed, get medical help or contact a Poison Control Center right away.

Directions

- wet hands thoroughly with product and allow to dry without wiping

Inactive ingredient

Purified water